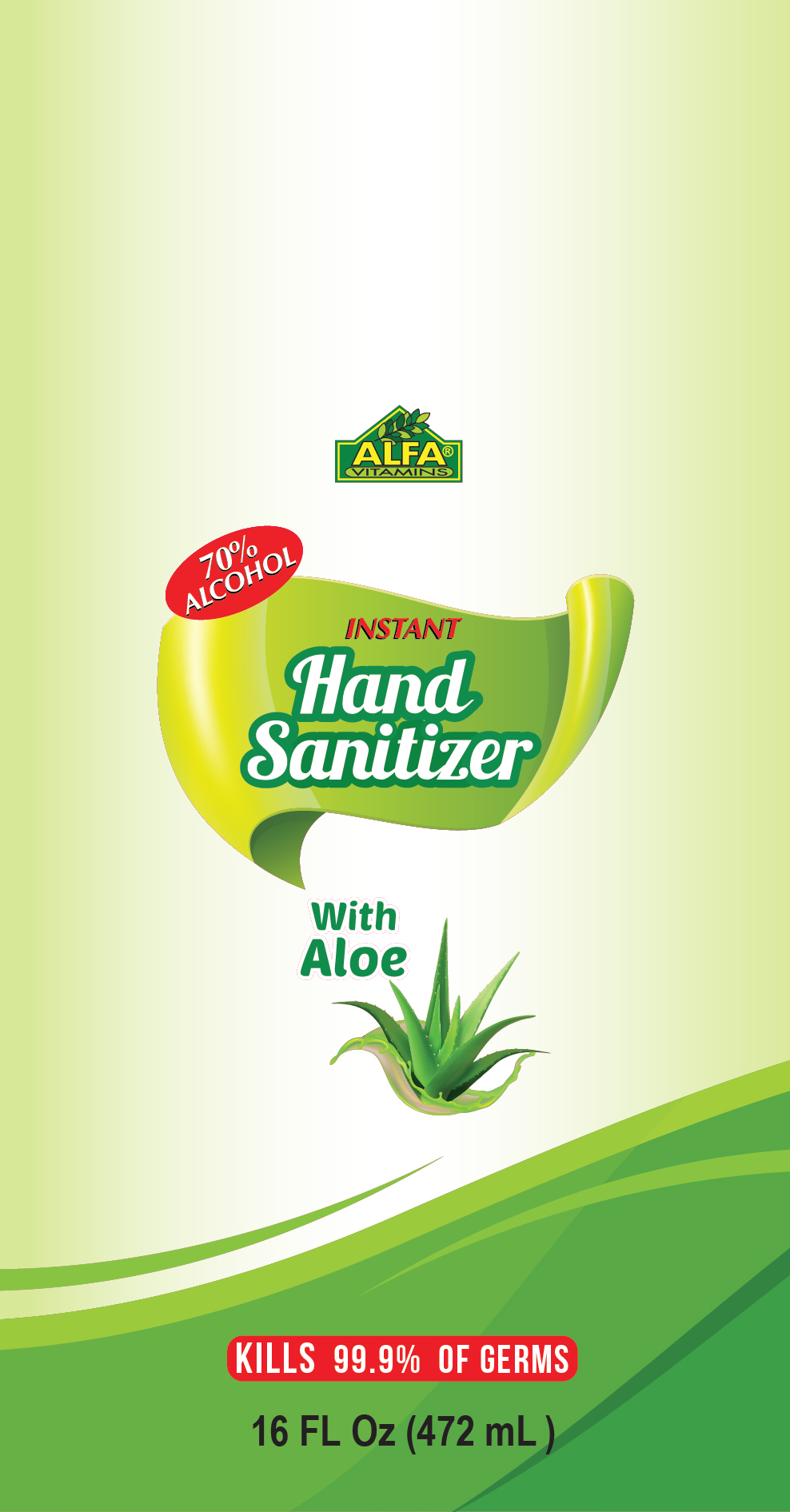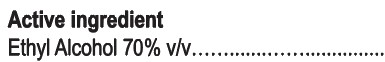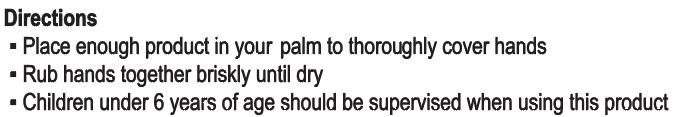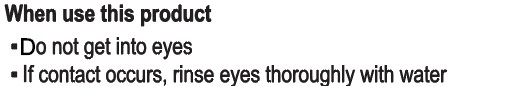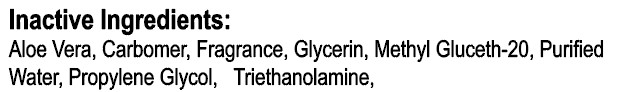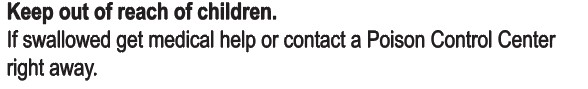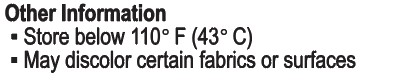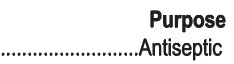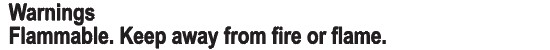 DRUG LABEL: Hand Sanitizer
NDC: 13298-156 | Form: JELLY
Manufacturer: ALFA VITAMINS LABORATORIES INC
Category: otc | Type: HUMAN OTC DRUG LABEL
Date: 20200923

ACTIVE INGREDIENTS: ALCOHOL 75 mL/100 mL
INACTIVE INGREDIENTS: PROPYLENE GLYCOL 99.8 mL/100 mL; GLYCERIN 1.45 mL/100 mL; WATER; METHYL GLUCETH-20 99 mL/100 mL; CARBOMER 940 99 mL/100 mL; FRAGRANCE CLEAN ORC0600327 99 mL/100 mL; ALOE VERA WHOLE 25 mL/100 mL; TRIETHANOLAMINE DODECYLBENZENESULFONATE 99 mL/100 mL

This is a hand sanitizer manufactured according to the Temporary Policy for Preparation of Certain Alcohol-Based Hand Sanitizer Products During the Public Health Emergency (CoViD-19); Guidance for Industry.

The hand sanitizer is manufactured using only the following United States Pharmacopoeia (USP) grade ingredients in the preparation of the product (percentage in final product formulation) consistent with World Health Organization (WHO) recommendations:

1. Alcohol (ethanol) (USP or Food Chemical Codex (FCC) grade) (80%, volume/volume (v/v)) in an aqueous solution denatured according to Alcohol and Tobacco Tax and Trade Bureau regulations in 27 CFR part 20.
2. Glycerol (1.45% v/v).
3. Hydrogen peroxide (0.125% v/v).
4. Sterile distilled water or boiled cold water.

The firm does not add other active or inactive ingredients. Different or additional ingredients may impact the quality and potency of the product.

Active Ingredient(s)

Alcohol 70% v/v. Purpose: Antiseptic

Purpose

Antiseptic, Hand Sanitizer

DIRECTIONS

Place enough product in your to thoroughly covere hands

Rub hands together briskly until mdry

Children under 6 years of age should be supervised when using the product

Warnings

For external use only. Flammable. Keep away from heat or flame

Do not use

- Do not get into eyes
- If contact occurs, rinse eyes throughly with water

WHEN USING

Do not get into eyes

If contact occurs, rinse eyes throughly with water

STOP USE

Irritation or rash appears and lasts

Keep out of reach of children. If swallowed, get medical help or contact a Poison Control Center right away.

Directions

- Place enough product in your palm to thoroughly cover hands
- Rub hands together briskly until dry
- Children under 6 years of age should be supervised when using this product

Other information

- Store below 110F (43C)
- May discolor certain fabrics or surfaces

Inactive ingredients

Aloe Vera, Carbomer, Fragrance, Glycerin, Methyl Gluceth-20, Purief Water, Propylene Glycol, Triethanolamine

Package Label - Principal Display Panel

472 mL NDC: 13298-156-16